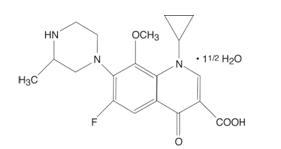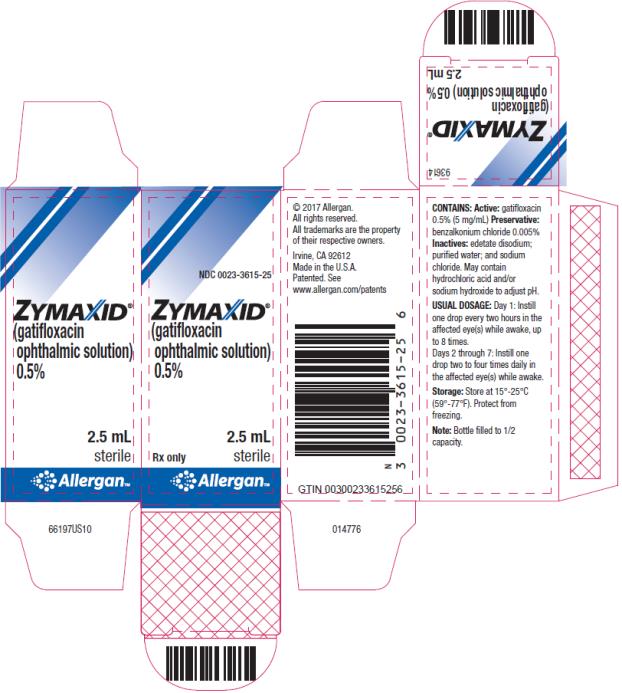 DRUG LABEL: ZYMAXID
NDC: 0023-3615 | Form: SOLUTION/ DROPS
Manufacturer: Allergan, Inc.
Category: prescription | Type: HUMAN PRESCRIPTION DRUG LABEL
Date: 20160901

ACTIVE INGREDIENTS: GATIFLOXACIN 5 mg/1 mL
INACTIVE INGREDIENTS: EDETATE DISODIUM; WATER; SODIUM CHLORIDE; BENZALKONIUM CHLORIDE; HYDROCHLORIC ACID; SODIUM HYDROXIDE

HIGHLIGHTS OF PRESCRIBING INFORMATION

These highlights do not include all the information needed to use ZYMAXID® safely and effectively. See full prescribing information for ZYMAXID®.
ZYMAXID® (gatifloxacin ophthalmic solution) 0.5% for topical ophthalmic use
Initial U.S. Approval: 1999

RECENT MAJOR CHANGES

Contraindications, Hypersensitivity (4) | 09/2016
Warnings and Precautions, Hypersensitivity (5.1) | 09/2016

1 INDICATIONS AND USAGE

ZYMAXID® is a quinolone antimicrobial indicated for the treatment of bacterial conjunctivitis caused by susceptible strains of the following organisms:

Haemophilus influenzae, Staphylococcus aureus, Staphylococcus epidermidis, Streptococcus mitis group, Streptococcus oralis, Streptococcus pneumoniae (1)

2 DOSAGE AND ADMINISTRATION

Day 1: Instill one drop every two hours in the affected eye(s) while awake, up to 8 times on Day 1.

Days 2 through 7: Instill one drop two to four times daily in the affected eye(s) while awake on Days 2 through 7. (2)

3 DOSAGE FORMS AND STRENGTHS

Ophthalmic solution: 0.5% gatifloxacin (5mg/mL) (3)

4 CONTRAINDICATIONS

ZYMAXID® is contraindicated in patients with a history of hypersensitivity to gatifloxacin, to other quinolones, or to any of the components in this medication. (4)

5 WARNINGS AND PRECAUTIONS

- Hypersensitivity (5.1)
- Growth of Resistant Organisms with Prolonged Use (5.2)
- Corneal Endothelial Cell Injury (5.3)

6 ADVERSE REACTIONS

Most common adverse reactions occurring in ≥ 1 % of patients included worsening of conjunctivitis, eye irritation, dysgeusia, and eye pain. (6)

To report SUSPECTED ADVERSE REACTIONS, contact Allergan at 1-800-433-8871 or FDA at 1-800-FDA-1088 or www.fda.gov/medwatch.

FULL PRESCRIBING INFORMATION

1 INDICATIONS AND USAGE

ZYMAXID® is indicated for the treatment of bacterial conjunctivitis caused by susceptible strains of the following organisms:

- Aerobic gram-positive bacteria:
  Staphylococcus aureus
  Staphylococcus epidermidis
  Streptococcus mitis group*
  Streptococcus oralis*
  Streptococcus pneumoniae

- Aerobic gram-negative bacteria:
  Haemophilus influenzae

*Efficacy for these organisms were studied in fewer than 10 infections.

2 DOSAGE AND ADMINISTRATION

- Day 1: Instill one drop every two hours in the affected eye(s) while awake, up to 8 times.
- Day 2 through Day 7: Instill one drop two to four times daily in the affected eye(s) while awake.

3 DOSAGE FORMS AND STRENGTHS

Ophthalmic solution: 0.5% gatifloxacin (5 mg/mL)

4 CONTRAINDICATIONS

ZYMAXID® is contraindicated in patients with a history of hypersensitivity to gatifloxacin, to other quinolones, or to any of the components in this medication [see Warnings and Precautions (5.1)].

5 WARNINGS AND PRECAUTIONS

5.1 Hypersensitivity

Some patients receiving topical ophthalmic gatifloxacin experienced hypersensitivity reactions including anaphylactic reactions, angioedema (including pharyngeal, laryngeal, or facial edema), dyspnea, urticaria, and itching, even following a single dose. Rare cases of Stevens-Johnson Syndrome were reported in association with topical ophthalmic gatifloxacin use. If an allergic reaction to gatifloxacin occurs, discontinue the drug [see Patient Counseling Information (17)].

5.2 Growth of Resistant Organisms with Prolonged Use

Prolonged use of ZYMAXID® may result in overgrowth of nonsusceptible organisms, including fungi. If superinfection occurs, discontinue use and institute alternative therapy. Whenever clinical judgment dictates, examine the patient with the aid of magnification, such as slit lamp biomicroscopy and where appropriate, fluorescein staining.

5.3 Corneal Endothelial Cell Injury

ZYMAXID® is for topical ophthalmic use. ZYMAXID® may cause corneal endothelial cell injury if introduced directly into the anterior chamber of the eye.

6 ADVERSE REACTIONS

The following serious adverse reactions are described elsewhere in the labeling:

- Hypersensitivity [see Contraindications (4) and Warnings and Precautions (5.1)]
- Growth of Resistant Organisms With Prolonged Use [see Warnings and Precautions (5.2)]
- Corneal Endothelial Cell Injury [see Warnings and Precautions (5.3)]

6.1 Clinical Studies Experience

Because clinical studies are conducted under widely varying conditions, adverse reaction rates observed in the clinical studies of a drug cannot be directly compared to rates in the clinical studies of another drug and may not reflect the rates observed in practice.

In clinical studies of patients with bacterial conjunctivitis treated with ZYMAXID® (N=717), the most frequently reported adverse reactions occurring in ≥ 1 % of patients were: worsening of the conjunctivitis, eye irritation, dysgeusia, and eye pain.

Additional adverse reactions reported with other formulations of gatifloxacin ophthalmic solution in other clinical studies included chemosis, conjunctival hemorrhage, dry eye, eye discharge, eyelid edema, headache, increased lacrimation, keratitis, red eye, papillary conjunctivitis, and reduced visual acuity.

6.2 Postmarketing Experience

The following adverse reactions have been identified during post-approval use of ZYMAXID® or with other formulations of gatifloxacin ophthalmic solution. Because these reactions are reported voluntarily from a population of uncertain size, it is not always possible to reliably estimate their frequency or establish a causal relationship to drug exposure. These reactions included anaphylactic reactions and angioedema (including pharyngeal, oral or facial edema), blepharitis, dyspnea, eye pruritus, eye swelling (including corneal and conjunctival edema), hypersensitivity, including signs and symptoms of eye allergy and allergic dermatitis, nausea, pruritus (including pruritus generalized, rash, urticaria), and vision blurred.

8 USE IN SPECIFIC POPULATIONS

8.1 Pregnancy

Risk Summary
There are no available data on the use of ZYMAXID® in pregnant women to inform a drug-associated risk. Administration of oral gatifloxacin to pregnant rats and rabbits throughout organogenesis did not produce adverse development outcomes at clinically relevant doses. Administration of gatifloxacin to rats during late gestation through lactation did not produce adverse maternal, fetal or neonatal effects at clinically relevant doses.

Data
Animal Data
Oral administration of gatifloxacin to pregnant rats throughout organogenesis produced teratogenic effects in rat fetuses, including skeletal/craniofacial malformations, delayed ossification, atrial enlargement, and reduced fetal weight, at doses greater than or equal to 150 mg/kg/day (approximately 600-fold higher than the maximum recommended human ophthalmic dose [MRHOD] for ZYMAXID® of 0.04 mg/kg/day, on a mg/m^2 basis). No teratogenic effects were observed in rat or rabbit fetuses at doses of gatifloxacin up to 50 mg/kg/day (approximately 200- and 400-fold higher than the MRHOD, respectively, on a mg/m^2 basis).

In a perinatal/postnatal study in rats, oral administration of gatifloxacin during late gestation through lactation produced an increase in late gestation fetal loss and neonatal/perinatal mortality at 200 mg/kg/day (approximately 800-fold higher than the MRHOD on a mg/m^2 basis).

8.2 Lactation

Risk Summary
There is no information regarding the presence of ZYMAXID® in human milk, the effect of gatifloxacin on breastfed infants, or the effect of gatifloxacin on milk production. Gatifloxacin was found in the breast milk of rats following oral administration of gatifloxacin during lactation. However, systemic levels of gatifloxacin following topical ocular administration are low [see Clinical Pharmacology (12.3)], and it is not known whether gatifloxacin would be present in maternal milk at measurable levels following topical ocular administration. The developmental and health benefits of breastfeeding should be considered along with the mother’s clinical need for ZYMAXID® and any potential adverse effects on the breastfed child from ZYMAXID®.

8.4 Pediatric Use

The safety and effectiveness of ZYMAXID® in infants below one year of age have not been established. ZYMAXID® has been demonstrated in clinical trials to be safe and effective for the treatment of bacterial conjunctivitis in pediatric patients one year or older [see Clinical Studies (14)].

8.5 Geriatric Use

No overall differences in safety or effectiveness have been observed between elderly and younger patients.

11 DESCRIPTION

ZYMAXID® is a quinolone antimicrobial topical ophthalmic solution for the treatment of bacterial conjunctivitis. Its chemical name is (±)-1-Cyclopropyl-6-fluoro-1,4-dihydro-8-methoxy-7-(3-methyl-1-piperazinyl)-4-oxo-3-quinolinecarboxylic acid, sesquihydrate. Its molecular formula is C19H22FN3O4 · 1½ H2O and its molecular weight is 402.42. Its chemical structure is:

ZYMAXID® is a clear, pale yellow, sterile, preserved aqueous solution with an osmolality of 260-330 mOsm/kg and a pH of 5.1-5.7.

ZYMAXID® contains the active ingredient gatifloxacin 0.5% (5 mg/mL) and the inactive ingredients benzalkonium chloride 0.005%, edetate disodium, sodium chloride and purified water. ZYMAXID® may contain hydrochloric acid and/or sodium hydroxide to adjust pH.

12 CLINICAL PHARMACOLOGY

12.1 Mechanism of Action

Gatifloxacin is a quinolone antimicrobial [see Microbiology (12.4)].

12.3 Pharmacokinetics

Gatifloxacin ophthalmic solution 0.5% was administered to one eye of 6 healthy male subjects each in an escalated dosing regimen starting with a single 2 drop dose, then 2 drops 4 times daily for 7 days, and finally 2 drops 8 times daily for 3 days. At all time points, serum gatifloxacin levels were below the lower limit of quantification (5 ng/mL) in all subjects.

12.4 Microbiology

Gatifloxacin is an 8-methoxyfluoroquinolone with a 3-methylpiperazinyl substituent at C7. The antibacterial action of gatifloxacin results from inhibition of DNA gyrase and topoisomerase IV. DNA gyrase is an essential enzyme that is involved in the replication, transcription, and repair of bacterial DNA. Topoisomerase IV is an enzyme known to play a key role in the partitioning of the chromosomal DNA during bacterial cell division. The mechanism of action of fluoroquinolones including gatifloxacin is different from that of aminoglycoside, macrolide, and tetracycline antibiotics. Therefore, gatifloxacin may be active against pathogens that are resistant to these antibiotics and these antibiotics may be active against pathogens that are resistant to gatifloxacin. There is no cross-resistance between gatifloxacin and the aforementioned classes of antibiotics. Cross-resistance has been observed between systemic gatifloxacin and some other fluoroquinolones.

Resistance to gatifloxacin in vitro develops via multiple-step mutations. Resistance to gatifloxacin in vitro occurs at a general frequency of 1 x 10^-7 to 10^-10.

Gatifloxacin has been shown to be active against most isolates of the following organisms both microbiologically and clinically, in conjunctival infections:

- Aerobic gram-positive bacteria:
  Staphylococcus aureus
  Staphylococcus epidermidis
  Streptococcus mitis group*
  Streptococcus oralis*
  Streptococcus pneumoniae

- Aerobic gram-negative bacteria:
  Haemophilus influenzae

*Efficacy for these organisms were studied in fewer than 10 infections.

13 NONCLINICAL TOXICOLOGY

13.1 Carcinogenesis, Mutagenesis, Impairment of Fertility

Carcinogenesis
There was no increase in neoplasms among B6C3F1 mice given gatifloxacin in the diet for 18 months at doses averaging 81 mg/kg/day in males and 90 mg/kg/day in females. These doses are approximately 175-fold higher than the maximum recommended ophthalmic dose (MRHOD) of 0.04 mg/kg/day ZYMAXID® in a 60 kg human (on a mg/m^2 basis).

A statistically significant increase in the incidence of large granular lymphocyte (LGL) leukemia was seen in male rats treated with 100 mg/kg/day (approximately 405-fold higher than the MRHOD, on a mg/m^2 basis). Fischer 344 rats have a high spontaneous background rate of LGL leukemia and the incidence in high-dose males only slightly exceeded the historical control range established for this strain. There was no increase in neoplasms among Fischer 344 rats given gatifloxacin in the diet for 2 years at doses averaging 47 mg/kg/day in males and 139 mg/kg/day in females (approximately 190- and 560-fold higher than the MRHOD, respectively), on a mg/m^2 basis.

Mutagenesis
In genetic toxicity tests, gatifloxacin was positive in 1 of 5 strains used in bacterial reverse mutation assays: Salmonella strain TA102. Gatifloxacin was positive in in vitro mammalian cell mutation and chromosome aberration assays. Gatifloxacin was positive in in vitro unscheduled DNA synthesis in rat hepatocytes but not human leukocytes. Gatifloxacin was negative in in vivo micronucleus tests in mice, cytogenetics test in rats, and DNA repair test in rats. The genotoxic findings are similar to findings obtained with other quinolones and may be due to the pharmacologic inhibitory effects of high concentrations of gatifloxacin on eukaryotic type II DNA topoisomerase.

Impairment of Fertility
Oral administration of gatifloxacin produced no adverse effects on fertility or reproduction in rats at doses up to 200 mg/kg/day (approximately 800-fold higher than the MRHOD, on a mg/m^2 basis).

14 CLINICAL STUDIES

In two randomized, double-masked, multicenter clinical trials, where patients 1-89 years of age were dosed for 5 days, ZYMAXID® was clinically superior to its vehicle on day 6 in patients with conjunctivitis and positive conjunctival cultures. Clinical outcomes for the trials demonstrated clinical success (resolution of conjunctival hyperemia and conjunctival discharge) in 58% (193/333) of patients for the gatifloxacin-treated groups versus 45% (148/325) for the vehicle-treated groups. Microbiological outcomes for the same clinical trials demonstrated a statistically superior eradication rate for causative pathogens of 90% (301/333) for gatifloxacin vs. 70% (228/325) for vehicle. Please note that microbiological eradication does not always correlate with clinical outcome in anti-infective trials.

16 HOW SUPPLIED/STORAGE AND HANDLING

ZYMAXID® (gatifloxacin ophthalmic solution) 0.5% is supplied sterile in a white, low density polyethylene (LDPE) bottle with a controlled dropper tip, and a tan, high impact polystyrene (HIPS) cap in the following size:

2.5 mL in 5 mL bottle: NDC 0023-3615-25

Storage: Store at 15°-25°C (59°-77°F). Protect from freezing.

17 PATIENT COUNSELING INFORMATION

Avoiding Contamination of the Product
Instruct patients to avoid contaminating the applicator tip with material from the eye, fingers, or other source.

Potential for Hypersensitivity Reactions
Advise patients to discontinue use immediately and contact the physician at the first sign of a rash or hypersensitivity reaction [see Warnings and Precautions (5.1) and Contraindication (4)].

© 2017 Allergan. All rights reserved.

All trademarks are the property of their respective owners.

Patented. See www.allergan.com/patents
Irvine, CA 92612
Made in the U.S.A.

72366US14

PACKAGE LABEL

PRINCIPAL DISPLAY PANEL
NDC 0023-3615-25
ZYMAXID
(gatifloxacin ophthalmic solution)
0.5%
2.5 mL
Rx Only Sterile